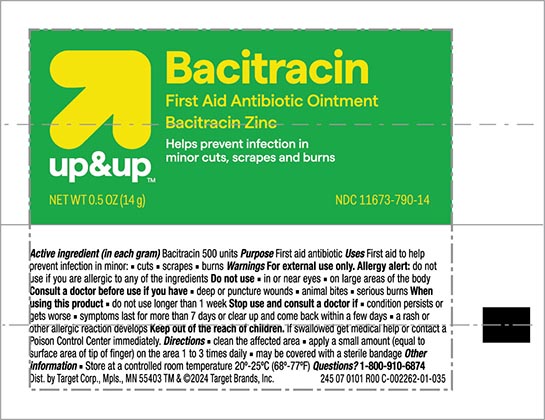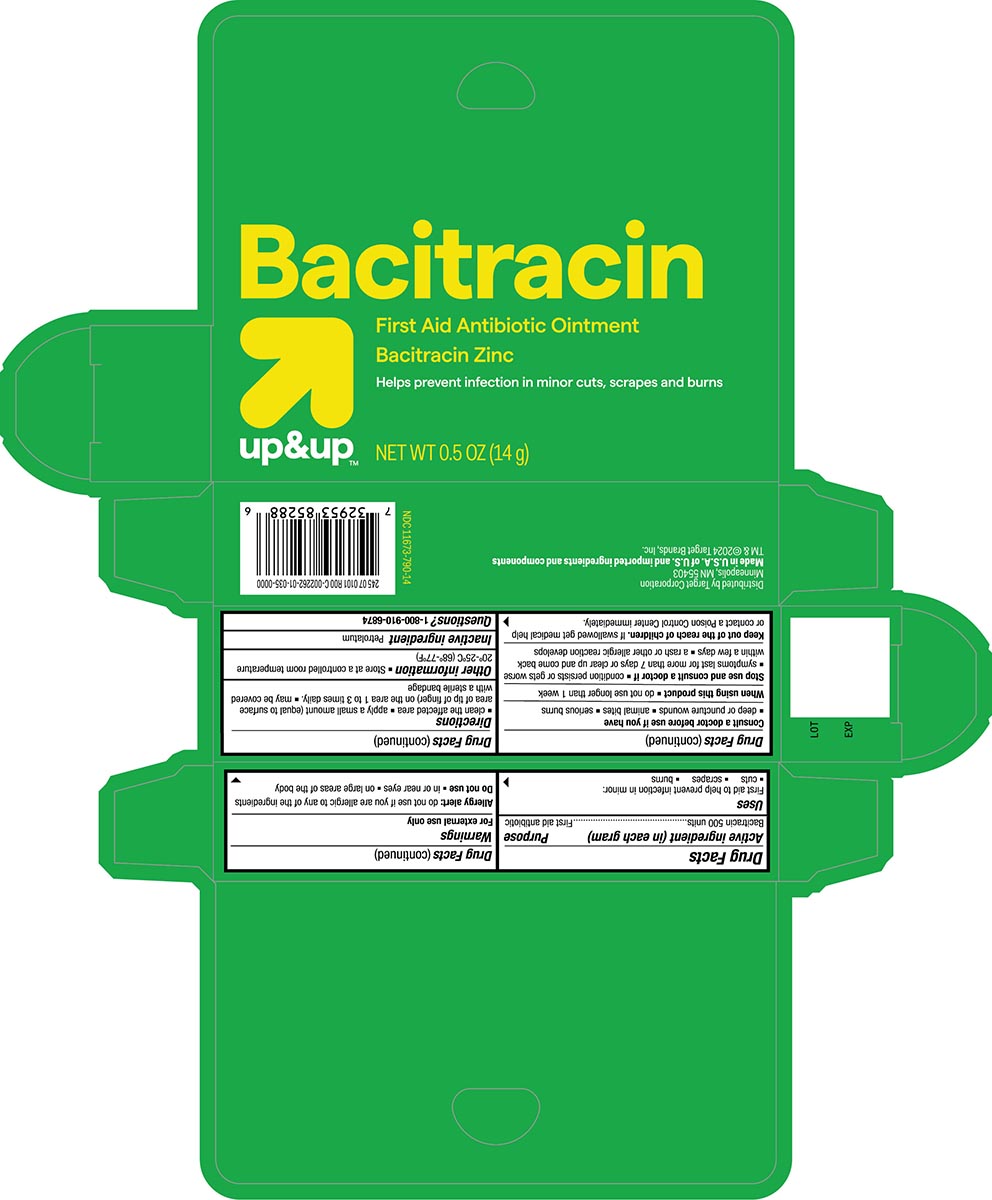 DRUG LABEL: First Aid Antibiotic
NDC: 11673-790 | Form: OINTMENT
Manufacturer: Target Corporation
Category: otc | Type: HUMAN OTC DRUG LABEL
Date: 20240117

ACTIVE INGREDIENTS: BACITRACIN ZINC 500 [USP'U]/1 g
INACTIVE INGREDIENTS: PETROLATUM

Target Up &Up First Aid Antibiotic Ointment

Active Ingredient

Bacitracin 500 units

Uses

Bacitracin -First Aid Antibiotic

Uses

First aid to help prevent infection in minor:

- cuts
- scrapes
- burns

Warnings

For external use only

Allergy alert do not use if you are allergic to any of the ingredients

Do not use

- in or near eyes
- on large arteas of the body

Consult a doctor before use if you have

- deep puncture wounds
- animal bites
- serious burns

When using this product

- do not use longer than 1 week

Stop use and consult a doctor if

- condition persists or gets worse
- symptoms last for more than 7 days or clear up and come back within a few days
- a rash or other allergic reaction develops

Keep out of the reach of children

If swallowed get medical help or contact a Poison Control Center immediately.

Directions

- clean the affected area
- apply a small amount (equal to surface area of tip of finger) on the area 1 to 3 times daily.
- may be covered with a sterile bandage

Other information

Store at a controlled room temperature 20º-25ºC (68° to 77°F)

Inactive ingredient

Petrolatum

Principal Display Panel

Target Up and Up NDC 11673-790-14

Bacitracin ointment

First aid Antibiotic Ointment

NET WT 0.5OZ (14g)